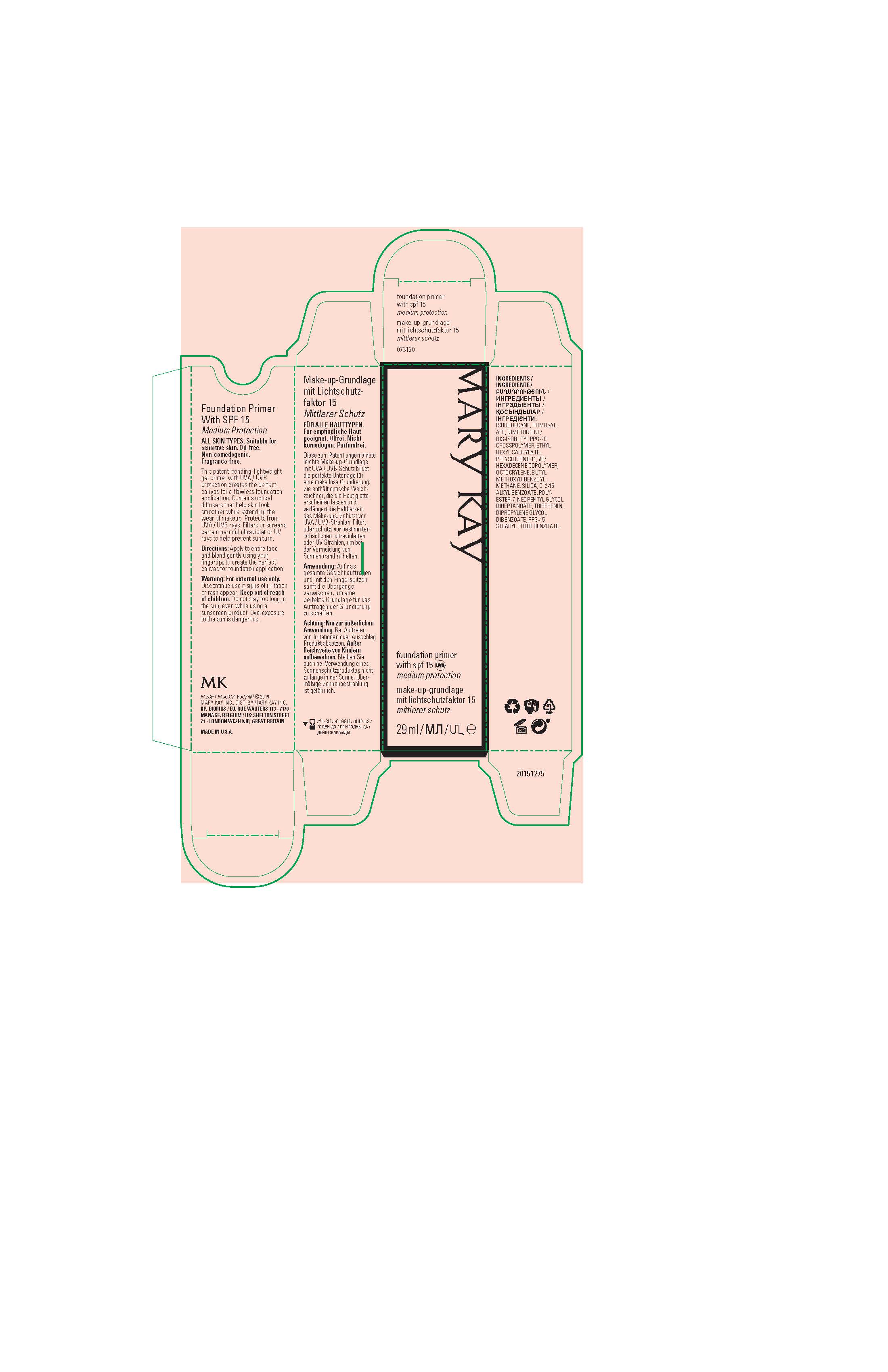 DRUG LABEL: Mary Kay Foundation Primer with SPF 15
NDC: 51531-3120 | Form: GEL
Manufacturer: Mary Kay Inc.
Category: otc | Type: HUMAN OTC DRUG LABEL
Date: 20221010

ACTIVE INGREDIENTS: OCTISALATE 5 g/100 mL; OCTOCRYLENE 3 g/100 mL; AVOBENZONE 2.5 g/100 mL; HOMOSALATE 9 g/100 mL
INACTIVE INGREDIENTS: DIMETHICONE/VINYL DIMETHICONE CROSSPOLYMER (SOFT PARTICLE); ISODODECANE; DIMETHICONE/BIS-ISOBUTYL PPG-20 CROSSPOLYMER; SILICON DIOXIDE; NEOPENTYL GLYCOL DIHEPTANOATE; TRIBEHENIN; DIPROPYLENE GLYCOL DIBENZOATE; PPG-15 STEARYL ETHER BENZOATE; VINYLPYRROLIDONE/HEXADECENE COPOLYMER; ALKYL (C12-15) BENZOATE; POLYESTER-7

Mary Kay Foundation Primer with SPF 15 EU Export Only

INDICATIONS AND USAGE

This patent-pending, lightweight gel primer with UVA / UVB protection creates the perfect
canvas for a flawless foundation application.

Contains optical diffusers that help skin look smoother while extending the wear of makeup.

Protects from UVA / UVB rays.

Filters or screens certain harmful ultraviolet or UV rays to help prevent sunburn.

Directions:

Apply to entire face and blend gently using your fingertips to create the perfect canvas for foundation application.

Warnings:

For external use only.
Discontinue use if signs of irritation or rash appear.

Keep out of reach of children.

Do not stay too long in the sun, even while using a sunscreen product.

Overexposure to the sun is dangerous.

Ingredients:

ISODODECANE, HOMOSALATE, DIMETHICONE/BIS-ISOBUTYL PPG-20 CROSSPOLYMER,

ETHYLHEXYL SALICYLATE, POLYSILICONE-11, VP/HEXADECENE COPOLYMER,

OCTOCRYLENE, BUTYL METHOXYDIBENZOYLMETHANE, SILICA, C12-15
ALKYL BENZOATE, POLYESTER-7, NEOPENTYL GLYCOL DIHEPTANOATE, TRIBEHENIN,
DIPROPYLENE GLYCOL DIBENZOATE, PPG-15 STEARYL ETHER BENZOATE.

Principal Display Panel - 29 mL carton

Mary Kay

foundation primer with spf 15

medium protection

29 ml